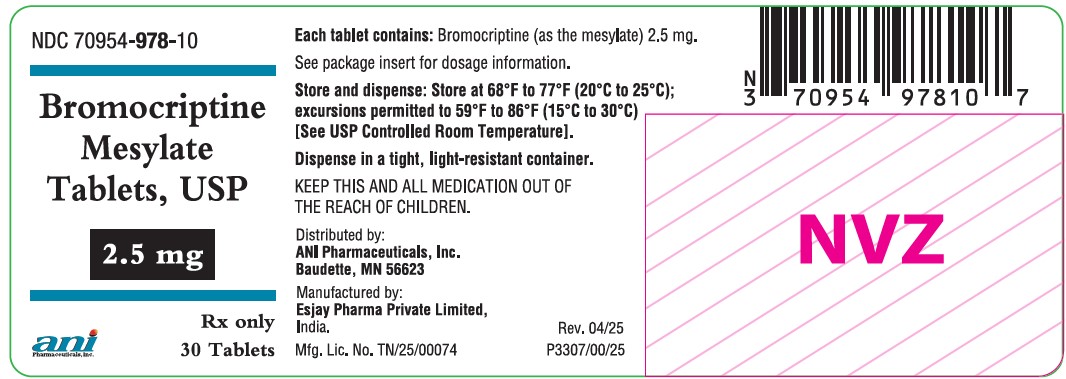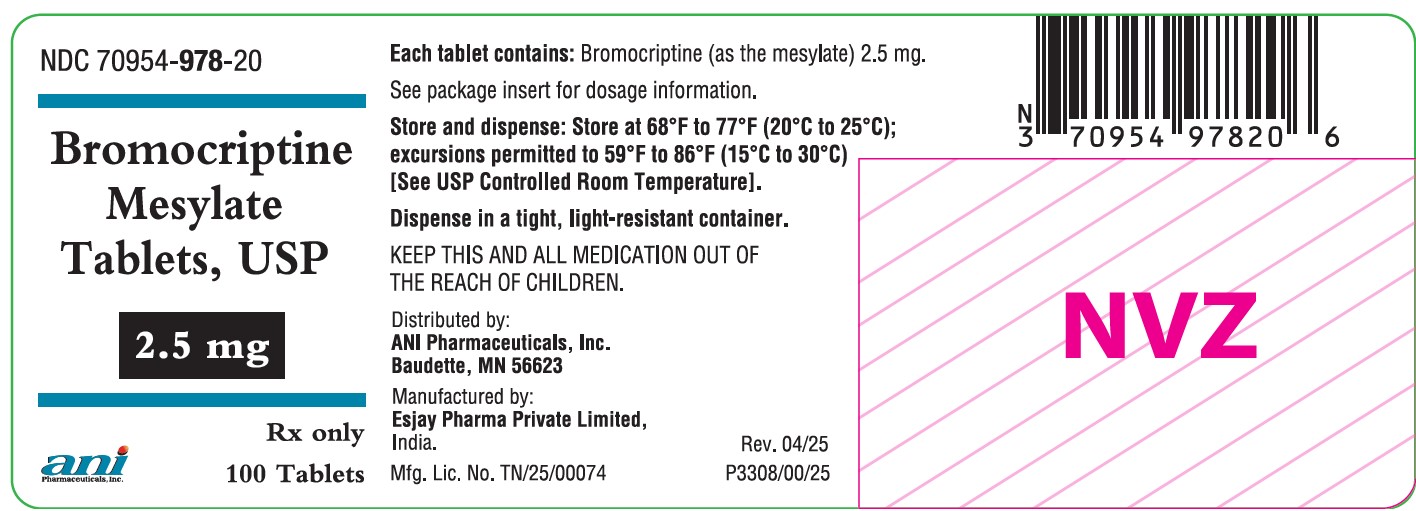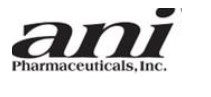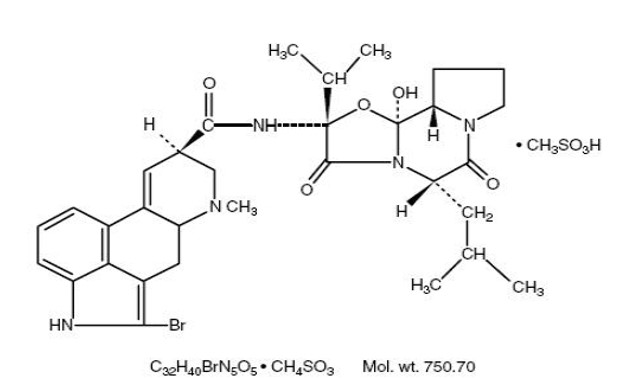 DRUG LABEL: Bromocriptine Mesylate
NDC: 70954-978 | Form: TABLET
Manufacturer: ANI Pharmaceuticals, Inc.
Category: prescription | Type: Human Prescription Drug Label
Date: 20250611

ACTIVE INGREDIENTS: BROMOCRIPTINE MESYLATE 2.5 mg/1 1
INACTIVE INGREDIENTS: SILICON DIOXIDE; LACTOSE MONOHYDRATE; MAGNESIUM STEARATE; MALEIC ACID; STARCH, CORN; POVIDONE K30

Bromocriptine Mesylate Tablets, USP
Rx Only
Prescribing Information

DESCRIPTION

Bromocriptine mesylate is an ergot derivative with potent dopamine receptor agonist activity. Each bromocriptine mesylate tablet for oral administration contains 2.5 mg bromocriptine (as the mesylate). Bromocriptine mesylate is chemically designated as Ergotaman-3′, 6′, 18- trione, 2-bromo-12′- hydroxy-2′-(1-methylethyl)-5′-(2-methylpropyl)-,(5′α) -monomethanesulfonate (salt).

The structural formula is:

2.5 mg Tablets

Active Ingredient: bromocriptine mesylate, USP

Inactive Ingredients: colloidal silicon dioxide, lactose monohydrate, magnesium stearate, maleic acid, povidone, and corn starch.

Meets USP Dissolution Test 1.

CLINICAL PHARMACOLOGY

Bromocriptine mesylate is a dopamine receptor agonist, which activates post-synaptic dopamine receptors. The dopaminergic neurons in the tuberoinfundibular process modulate the secretion of prolactin from the anterior pituitary by secreting a prolactin inhibitory factor (thought to be dopamine); in the corpus striatum the dopaminergic neurons are involved in the control of motor function. Clinically, bromocriptine mesylate significantly reduces plasma levels of prolactin in patients with physiologically elevated prolactin as well as in patients with hyperprolactinemia. The inhibition of physiological lactation as well as galactorrhea in pathological hyperprolactinemic states is obtained at dose levels that do not affect secretion of other tropic hormones from the anterior pituitary. Experiments have demonstrated that bromocriptine induces long-lasting stereotyped behavior in rodents and turning behavior in rats having unilateral lesions in the substantia nigra. These actions, characteristic of those produced by dopamine, are inhibited by dopamine antagonists and suggest a direct action of bromocriptine on striatal dopamine receptors.

Bromocriptine mesylate is a nonhormonal, nonestrogenic agent that inhibits the secretion of prolactin in humans, with little or no effect on other pituitary hormones, except in patients with acromegaly, where it lowers elevated blood levels of growth hormone in the majority of patients.

Bromocriptine mesylate produces its therapeutic effect in the treatment of Parkinson’s disease, a clinical condition characterized by a progressive deficiency in dopamine synthesis in the substantia nigra, by directly stimulating the dopamine receptors in the corpus striatum. In contrast, levodopa exerts its therapeutic effect only after conversion to dopamine by the neurons of the substantia nigra, which are known to be numerically diminished in this patient population.

Pharmacokinetics

Absorption

Following single dose administration of bromocriptine mesylate tablets, 2 x 2.5 mg to 5 healthy volunteers under fasted conditions, the mean peak plasma levels of bromocriptine, time to reach peak plasma concentrations and elimination half-life were 465 pg/mL ± 226, 2.5 hrs ± 2 and 4.85 hr, respectively.^1 Linear relationship was found between single doses of bromocriptine mesylate and Cmax and AUC in the dose range of 1 to 7.5 mg.^2 The pharmacokinetics of bromocriptine metabolites have not been reported.

Food did not significantly affect the systemic exposure of bromocriptine following administration of bromocriptine mesylate tablets, 2.5 mg.^3 It is recommended that bromocriptine mesylate be taken with food because of the high percentage of subjects who vomit upon receiving bromocriptine under fasting conditions.

Following bromocriptine mesylate 5 mg administered twice daily for 14 days, the bromocriptine Cmax and AUC at steady-state were 628 ± 375 pg/mL and 2377 ± 1186 pg*hr/mL, respectively.^4

Distribution

In vitro experiments showed that bromocriptine was 90% - 96% bound to serum albumin.

Metabolism

Bromocriptine undergoes extensive first-pass biotransformation, reflected by complex metabolite profiles and by almost complete absence of parent drug in urine and feces.

In vitro studies using human liver microsomes showed that bromocriptine has a high affinity for CYP3A and hydroxylations at the proline ring of the cyclopeptide moiety constituted a main metabolic pathway.^5 Inhibitors and/or potent substrates for CYP3A4 might therefore inhibit the clearance of bromocriptine and lead to increased levels. (see PRECAUTIONS, drug interactions section). The participation of other major CYP enzymes such as 2D6, 2C8, and 2C19 on the metabolism of bromocriptine has not been evaluated. Bromocriptine is also an inhibitor of CYP3A4 with a calculated IC50 value of 1.69 μM.^6 Given the low therapeutic concentrations of bromocriptine in patients (Cmax=0.82 nM), a significant alteration of the metabolism of a second drug whose clearance is mediated by CYP3A4 should not be expected. The potential effect of bromocriptine and its metabolites to act as inducers of CYP enzymes has not been reported.

Excretion

About 82% and 5.6 % of the radioactive dose orally administered was recovered in feces and urine, respectively. Bromolysergic acid and bromoisolysergic acid accounted for half of the radioactivity in urine.^5

^1 Nelson, M. et. al. (1990). Pharmacokinetic evaluation of erythromycin and caffeine administered with bromocriptine. Clin Pharmacol Ther; 47(6):694-7.

^2 Schran, H.F., Bhuta, S.I., Schwartz, et al. (1980). The pharmacokinetics of bromocriptine in man. In: Golstein, M. Calne, D.B., et. Al (eds). Ergot compound and brain function: Neuroendocrine and neuropsychiatric aspects, pp. 125-139, New York, Rave Press.

^3 Kopitar, Z., Vrhovac, B., Povsic, L., Plavsic, F., Francetic, I., Urbancic, J. (1991). The effect of food and metoclopramide on the pharmacokinetics and side effects of bromocriptine. Eur J Drug Metab Pharmacokinet; 16(3):177-81

^4 Flogstad, A.K., Halse, J., Grass, P., Abisch, E., Djoseland, O., Kutz, K., Bodd, E., and Jervell, J., (1994). A comparison of octreotide, bromocriptine, or a combination of both drugs in acromegaly. Journal of Clinical Endocrinology & Metabolism; Vol 79, 461-465

^5 Peyronneau MA, Delaforge M, Riviere R et al. 1994. High affinity of ergopeptides for CYP P450 3A. Importance of their peptide moiety for P450 recognition and hydroxylation of bromocriptine. Eur J Biochem 223:947-56.

^6 Wynalda, M.A., Wienkers, L.C. (1997). Assessment of potential interactions between dopamine receptor agonists and various human cytochrome P450 enzymes using a simple in vitro inhibition screen. Drug Metab Dispos; 25:1211-14.

Specific Populations

Effect of Renal Impairment

The effect of renal function on the pharmacokinetics of bromocriptine has not been evaluated.

Since parent drug and metabolites are almost completely excreted via metabolism, and only 6% eliminated via the kidney, renal impairment may not have a significant impact on the PK of bromocriptine and its metabolites (see PRECAUTIONS, general).

Effect of Hepatic Impairment

The effect of liver impairment on the PK of bromocriptine mesylate and its metabolites has not been evaluated. Since bromocriptine mesylate is mainly eliminated by metabolism, liver impairment may increase the plasma levels of bromocriptine, therefore, caution may be necessary (see PRECAUTIONS, general).

The effect of age, race, and gender on the pharmacokinetics of bromocriptine and its metabolites has not been evaluated.

Clinical Studies

In about 75% of cases of amenorrhea and galactorrhea, bromocriptine mesylate therapy suppresses the galactorrhea completely, or almost completely, and reinitiates normal ovulatory menstrual cycles.

Menses are usually reinitiated prior to complete suppression of galactorrhea; the time for this on average is 6 to 8 weeks. However, some patients respond within a few days, and others may take up to 8 months.

Galactorrhea may take longer to control depending on the degree of stimulation of the mammary tissue prior to therapy. At least a 75% reduction in secretion is usually observed after 8 to 12 weeks. Some patients may fail to respond even after 12 months of therapy.

In many acromegalic patients, bromocriptine mesylate produces a prompt and sustained reduction in circulating levels of serum growth hormone.

INDICATIONS & USAGE

Hyperprolactinemia-Associated Dysfunctions

Bromocriptine mesylate is indicated for the treatment of dysfunctions associated with hyperprolactinemia including amenorrhea with or without galactorrhea, infertility or hypogonadism. Bromocriptine mesylate treatment is indicated in patients with prolactin-secreting adenomas, which may be the basic underlying endocrinopathy contributing to the above clinical presentations. Reduction in tumor size has been demonstrated in both male and female patients with macroadenomas. In cases where adenectomy is elected, a course of bromocriptine mesylate therapy may be used to reduce the tumor mass prior to surgery.

Acromegaly

Bromocriptine mesylate therapy is indicated in the treatment of acromegaly. Bromocriptine mesylate therapy, alone or as adjunctive therapy with pituitary irradiation or surgery, reduces serum growth hormone by 50% or more in approximately ½ of patients treated, although not usually to normal levels.

Since the effects of external pituitary radiation may not become maximal for several years, adjunctive therapy with bromocriptine mesylate offers potential benefit before the effects of irradiation are manifested.

Parkinson’s Disease

Bromocriptine mesylate tablets are indicated in the treatment of the signs and symptoms of idiopathic or postencephalitic Parkinson’s disease. As adjunctive treatment to levodopa (alone or with a peripheral decarboxylase inhibitor), bromocriptine mesylate therapy may provide additional therapeutic benefits in those patients who are currently maintained on optimal dosages of levodopa, those who are beginning to deteriorate (develop tolerance) to levodopa therapy, and those who are experiencing “end of dose failure” on levodopa therapy. Bromocriptine mesylate therapy may permit a reduction of the maintenance dose of levodopa and, thus may ameliorate the occurrence and/or severity of adverse reactions associated with long-term levodopa therapy such as abnormal involuntary movements (e.g., dyskinesias) and the marked swings in motor function (“on-off” phenomenon). Continued efficacy of bromocriptine mesylate therapy during treatment of more than 2 years has not been established.

Data are insufficient to evaluate potential benefit from treating newly diagnosed Parkinson’s disease with bromocriptine mesylate. Studies have shown, however, significantly more adverse reactions (notably nausea, hallucinations, confusion and hypotension) in bromocriptine mesylate-treated patients than in levodopa/carbidopa-treated patients. Patients unresponsive to levodopa are poor candidates for bromocriptine mesylate therapy.

CONTRAINDICATIONS

Hypersensitivity to bromocriptine or to any of the excipients of bromocriptine mesylate, uncontrolled hypertension and sensitivity to any ergot alkaloids. In patients being treated for hyperprolactinemia, bromocriptine mesylate should be withdrawn when pregnancy is diagnosed (see PRECAUTIONS, Hyperprolactinemic States). In the event that bromocriptine mesylate is reinstituted to control a rapidly expanding macroadenoma (see PRECAUTIONS, Hyperprolactinemic States) and a patient experiences a hypertensive disorder of pregnancy, the benefit of continuing bromocriptine mesylate must be weighed against the possible risk of its use during a hypertensive disorder of pregnancy. When bromocriptine mesylate is being used to treat acromegaly, prolactinoma, or Parkinson’s disease in patients who subsequently become pregnant, a decision should be made as to whether the therapy continues to be medically necessary or can be withdrawn. If it is continued, the drug should be withdrawn in those who may experience hypertensive disorders of pregnancy (including eclampsia, preeclampsia, or pregnancy-induced hypertension) unless withdrawal of bromocriptine mesylate is considered to be medically contraindicated.

The drug should not be used during the postpartum period in women with a history of coronary artery disease and other severe cardiovascular conditions unless withdrawal is considered medically contraindicated. If the drug is used in the postpartum period, the patient should be observed with caution.

WARNINGS

Since hyperprolactinemia with amenorrhea/galactorrhea and infertility has been found in patients with pituitary tumors, a complete evaluation of the pituitary is indicated before treatment with bromocriptine mesylate.

If pregnancy occurs during bromocriptine mesylate administration, careful observation of these patients is mandatory. Prolactin-secreting adenomas may expand and compression of the optic or other cranial nerves may occur, emergency pituitary surgery becoming necessary. In most cases, the compression resolves following delivery. Reinitiation of bromocriptine mesylate treatment has been reported to produce improvement in the visual fields of patients in whom nerve compression has occurred during pregnancy. The safety of bromocriptine mesylate treatment during pregnancy to the mother and fetus has not been established.

Bromocriptine mesylate has been associated with somnolence, and episodes of sudden sleep onset, particularly in patients with Parkinson’s disease. Sudden onset of sleep during daily activities, in some cases without awareness or warning signs, has been reported. Patients must be informed of this and advised not to drive or operate machines during treatment with bromocriptine. Patients who have experienced somnolence and/or an episode of sudden sleep onset must not drive or operate machines. Furthermore, a reduction of dosage or termination of therapy may be considered.

Symptomatic hypotension can occur in patients treated with bromocriptine mesylate for any indication. In postpartum studies with bromocriptine mesylate, decreases in supine systolic and diastolic pressures of greater than 20 mm and 10 mm Hg, respectively, have been observed in almost 30% of patients receiving bromocriptine mesylate. On occasion, the drop in supine systolic pressure was as much as 50-59 mm of Hg.

Since, especially during the first days of treatment, hypotensive reactions may occasionally occur and result in reduced alertness, particular care should be exercised when driving a vehicle or operating machinery.

While hypotension during the start of therapy with bromocriptine mesylate occurs in some patients, in rare cases serious adverse events, including hypertension, myocardial infarction, seizures, stroke, have been reported in postpartum women treated with bromocriptine mesylate for the inhibition of lactation. Hypertension have been reported, sometimes at the initiation of therapy, but often developing in the second week of therapy; seizures have also been reported both with and without the prior development of hypertension; stroke have been reported mostly in postpartum patients whose prenatal and obstetric courses had been uncomplicated. Many of these patients experiencing seizures (including cases of status epilepticus) and/or strokes reported developing a constant and often progressively severe headache hours to days prior to the acute event. Some cases of strokes and seizures were also preceded by visual disturbances (blurred vision, and transient cortical blindness). Cases of acute myocardial infarction have also been reported.

Although a causal relationship between bromocriptine mesylate administration and hypertension, seizures, strokes, and myocardial infarction in postpartum women has not been established, use of the drug for prevention of physiological lactation, or in patients with uncontrolled hypertension is not recommended. In patients being treated for hyperprolactinemia, bromocriptine mesylate should be withdrawn when pregnancy is diagnosed (see PRECAUTIONS, Hyperprolactinemic States). In the event that bromocriptine mesylate is reinstituted to control a rapidly expanding macroadenoma (see PRECAUTIONS, Hyperprolactinemic States) and a patient experiences a hypertensive disorder of pregnancy, the benefit of continuing bromocriptine mesylate must be weighed against the possible risk of its use during a hypertensive disorder of pregnancy. When bromocriptine mesylate is being used to treat acromegaly or Parkinson’s disease in patients who subsequently become pregnant, a decision should be made as to whether the therapy continues to be medically necessary or can be withdrawn. If it is continued, the drug should be withdrawn in those who may experience hypertensive disorders of pregnancy (including eclampsia, preeclampsia, or pregnancy-induced hypertension) unless withdrawal of bromocriptine mesylate is considered to be medically contraindicated. Because of the possibility of an interaction between bromocriptine mesylate and other ergot alkaloids, the concomitant use of these medications is not recommended. Periodic monitoring of the blood pressure, particularly during the first weeks of therapy is prudent. If hypertension, severe, progressive, or unremitting headache (with or without visual disturbance), or evidence of CNS toxicity develops, drug therapy should be discontinued and the patient should be evaluated promptly. Particular attention should be paid to patients who have recently been treated or are on concomitant therapy with drugs that can alter blood pressure. Their concomitant use in the puerperium is not recommended.

Among patients on bromocriptine mesylate, particularly on long-term and high-dose treatment, pleural and pericardial effusions, as well as pleural and pulmonary fibrosis and constrictive pericarditis, have been reported. Patients with unexplained pleuropulmonary disorders should be examined thoroughly and discontinuation of bromocriptine mesylate therapy should be considered. In those instances in which bromocriptine mesylate treatment was terminated, the changes slowly reverted towards normal.

In a few patients on bromocriptine mesylate, particularly on long-term and high-dose treatment, retroperitoneal fibrosis has been reported. To ensure recognition of retroperitoneal fibrosis at an early reversible stage it is recommended that its manifestations (e.g., back pain, edema of the lower limbs, impaired kidney function) should be watched in this category of patients. Bromocriptine mesylate medication should be withdrawn if fibrotic changes in the retroperitoneum are diagnosed or suspected.

PRECAUTIONS

GENERAL

There have been reports of patients experiencing intense urges to gamble, increased sexual urges, intense urges to spend money uncontrollably, and/or other intense urges, and the inability to control these urges while taking one or more of the medications, including bromocriptine mesylate, that increase central dopaminergic tone. In some cases, although not all, these urges were reported to have stopped when the dose was reduced, or the medication was discontinued. Because patients may not recognize these behaviors as abnormal, it is important for prescribers to specifically ask patients or their caregivers about the development of new or increased gambling urges, sexual urges, uncontrolled spending, or other urges while being treated with bromocriptine mesylate for Parkinson’s disease or hyperprolactinemia-associated dysfunctions. Physicians should consider dose reduction or stopping the medication if a patient develops such urges while taking bromocriptine mesylate.

Safety and efficacy of bromocriptine mesylate have not been established in patients with renal or hepatic disease. Care should be exercised when administering bromocriptine mesylate therapy concomitantly with other medications known to lower blood pressure.

The drug should be used with caution in patients with a history of psychosis or cardiovascular disease. If acromegalic patients or patients with prolactinoma or Parkinson’s disease are being treated with bromocriptine mesylate during pregnancy, they should be cautiously observed, particularly during the postpartum period if they have a history of cardiovascular disease.

Patients with rare hereditary problems of galactose intolerance, severe lactase deficiency or glucose-galactose malabsorption should not take this medicine.

Hyperprolactinemic States

Visual field impairment is a known complication of macroprolactinoma. Effective treatment with bromocriptine mesylate leads to a reduction in hyperprolactinemia and often to a resolution of the visual impairment. In some patients, however, a secondary deterioration of visual fields may subsequently develop despite normalized prolactin levels and tumor shrinkage, which may result from traction on the optic chiasm which is pulled down into the now partially empty sella. In these cases, the visual field defect may improve on reduction of bromocriptine dosage while there is some elevation of prolactin and some tumor re-expansion. Monitoring of visual fields in patients with macroprolactinoma is therefore recommended for an early recognition of secondary field loss due to chiasmal herniation and adaptation of drug dosage.

The relative efficacy of bromocriptine mesylate versus surgery in preserving visual fields is not known. Patients with rapidly progressive visual field loss should be evaluated by a neurosurgeon to help decide on the most appropriate therapy.

Since pregnancy is often the therapeutic objective in many hyperprolactinemic patients presenting with amenorrhea/galactorrhea and hypogonadism (infertility), a careful assessment of the pituitary is essential to detect the presence of a prolactin-secreting adenoma. Patients not seeking pregnancy, or those harboring large adenomas, should be advised to use contraceptive measures, other than oral contraceptives, during treatment with bromocriptine mesylate. Since pregnancy may occur prior to reinitiation of menses, a pregnancy test is recommended at least every 4 weeks during the amenorrheic period, and, once menses are reinitiated, every time a patient misses a menstrual period. Treatment with bromocriptine mesylate tablets should be discontinued as soon as pregnancy has been established. Patients must be monitored closely throughout pregnancy for signs and symptoms that may signal the enlargement of a previously undetected or existing prolactin-secreting tumor. Discontinuation of bromocriptine mesylate treatment in patients with known macroadenomas has been associated with rapid regrowth of tumor and increase in serum prolactin in most cases.

Cerebrospinal fluid rhinorrhea has been observed in some patients with prolactin-secreting adenomas treated with bromocriptine mesylate.

Acromegaly

Cold-sensitive digital vasospasm has been observed in some acromegalic patients treated with bromocriptine mesylate. The response, should it occur, can be reversed by reducing the dose of bromocriptine mesylate and may be prevented by keeping the fingers warm. Cases of severe gastrointestinal bleeding from peptic ulcers have been reported, some fatal. Although there is no evidence that bromocriptine mesylate increases the incidence of peptic ulcers in acromegalic patients, symptoms suggestive of peptic ulcer should be investigated thoroughly and treated appropriately. Patients with a history of peptic ulcer or gastrointestinal bleeding should be observed carefully during treatment with bromocriptine mesylate.

Possible tumor expansion while receiving bromocriptine mesylate therapy has been reported in a few patients. Since the natural history of growth hormone-secreting tumors is unknown, all patients should be carefully monitored and, if evidence of tumor expansion develops, discontinuation of treatment and alternative procedures considered.

Parkinson’s Disease

Safety during long-term use for more than 2 years at the doses required for parkinsonism has not been established.

As with any chronic therapy, periodic evaluation of hepatic, hematopoietic, cardiovascular, and renal function is recommended. Symptomatic hypotension can occur and, therefore, caution should be exercised when treating patients receiving antihypertensive drugs.

High doses of bromocriptine mesylate may be associated with confusion and mental disturbances. Since parkinsonian patients may manifest mild degrees of dementia, caution should be used when treating such patients.

Bromocriptine mesylate administered alone or concomitantly with levodopa may cause hallucinations (visual or auditory). Hallucinations usually resolve with dosage reduction; occasionally, discontinuation of bromocriptine mesylate is required. Rarely, after high doses, hallucinations have persisted for several weeks following discontinuation of bromocriptine mesylate.

As with levodopa, caution should be exercised when administering bromocriptine mesylate to patients with a history of myocardial infarction who have a residual atrial, nodal, or ventricular arrhythmia.

Retroperitoneal fibrosis has been reported in a few patients receiving long-term therapy (2 to 10 years) with bromocriptine mesylate in doses ranging from 30-140 mg daily.

Epidemiological studies have shown that patients with Parkinson’s disease have a higher risk (2-approximately 6-fold higher) of developing melanoma than the general population. Whether the increased risk observed was due to Parkinson’s disease or other factors, such as drugs used to treat Parkinson’s disease, is unclear. For the reasons stated above, patients and providers are advised to monitor for melanomas frequently and on a regular basis when using bromocriptine mesylate for any indication. Ideally, periodic skin examinations should be performed by appropriately qualified individuals (e.g., dermatologists).

Discontinuation of bromocriptine mesylate should be undertaken gradually whenever possible, even if the patient is to remain on levodopa. A symptom complex resembling the neuroleptic malignant syndrome (characterized by elevated temperature, muscular rigidity, altered consciousness, and autonomic instability), with no other obvious etiology, has been reported in association with rapid dose reduction, withdrawal of, or changes in antiparkinsonian therapy.

Symptoms including apathy, anxiety, depression, fatigue, insomnia, sweating, and pain have been reported during taper or after discontinuation of dopamine agonists, including bromocriptine mesylate. These symptoms generally do not respond to levodopa. Prior to discontinuation of bromocriptine mesylate, patients should be informed about potential withdrawal symptoms, and closely monitored during and after discontinuation of bromocriptine mesylate. In case of severe withdrawal symptoms, re-administration of a dopamine agonist at the lowest effective dose may be considered.

INFORMATION FOR PATIENTS

During clinical trials, dizziness, drowsiness, faintness, fainting, and syncope have been reported early in the course of bromocriptine mesylate therapy. In postmarketing reports, bromocriptine mesylate has been associated with somnolence, and episodes of sudden sleep onset, particularly in patients with Parkinson’s disease. Sudden onset of sleep during daily activities, in some cases without awareness or warning signs, has been reported very rarely. All patients receiving bromocriptine mesylate should be cautioned with regard to engaging in activities requiring rapid and precise responses, such as driving an automobile or operating machinery.

Patients being treated with bromocriptine mesylate and presenting with somnolence and/or sudden sleep episodes must be advised not to drive or engage in activities where impaired alertness may put themselves or others at risk of serious injury or death (e.g., operating machines).

Patients receiving bromocriptine mesylate for hyperprolactinemic states associated with macroadenoma or those who have had previous transsphenoidal surgery should be told to report any persistent watery nasal discharge to their physician. Patients receiving bromocriptine mesylate for treatment of a macroadenoma should be told that discontinuation of drug may be associated with rapid regrowth of the tumor and recurrence of their original symptoms.

Patients and their caregivers should be alerted to the possibility that patients may experience intense urges to spend money uncontrollably, intense urges to gamble, increased sexual urges and other intense urges and the inability to control these urges while taking bromocriptine mesylate. Advise patients and their caregivers to inform their healthcare provider if they develop new or increased uncontrolled spending, gambling urges, sexual urges, or other urges while being treated with bromocriptine mesylate [see PRECAUTIONS].

Especially during the first days of treatment, hypotensive reactions may occasionally occur and result in reduced alertness, particular care should be exercised when driving a vehicle or operating machinery.

Advise patients to contact their healthcare provider if they wish to discontinue bromocriptine mesylate or decrease the dose of bromocriptine mesylate. Advise patients who have been prescribed a lower dose or who have been withdrawn from the drug to notify their healthcare provider if they have withdrawal symptoms such as fever, muscular rigidity, altered consciousness, apathy, anxiety, depression, fatigue, insomnia, sweating, or pain (see Precautions).

DRUG INTERACTIONS

The risk of using bromocriptine mesylate in combination with other drugs has not been systematically evaluated, but alcohol may potentiate the side effects of bromocriptine mesylate. Bromocriptine mesylate may interact with dopamine antagonists, butyrophenones, and certain other agents. Compounds in these categories result in a decreased efficacy of bromocriptine mesylate: phenothiazines, haloperidol, metoclopramide, and pimozide. Bromocriptine is a substrate of CYP3A4. Caution should therefore be used when co-administering drugs which are strong inhibitors of this enzyme (such as azole antimycotics, HIV protease inhibitors). The concomitant use of macrolide antibiotics such as erythromycin was shown to increase the plasma levels of bromocriptine (mean AUC and Cmax values increased 3.7-fold and 4.6-fold, respectively).^1 The concomitant treatment of acromegalic patients with bromocriptine and octreotide led to increased plasma levels of bromocriptine (bromocriptine AUC increased about 38%).^4 Concomitant use of bromocriptine mesylate with other ergot alkaloids is not recommended. Dose adjustment may be necessary in those cases where high doses of bromocriptine are being used (such as Parkinson’s disease indication).

CARCINOGENESIS & MUTAGENESIS & IMPAIRMENT OF FERTILITY

A 74-week study was conducted in mice using dietary levels of bromocriptine mesylate equivalent to oral doses of 10 and 50 mg/kg/day. A 100-week study in rats was conducted using dietary levels equivalent to oral doses of 1.7, 9.8, and 44 mg/kg/day. The highest doses tested in mice and rats were approximately 2.5 and 4.4 times, respectively, the maximum human dose administered in controlled clinical trials (100 mg/day) based on body surface area. Malignant uterine tumors, endometrial and myometrial, were found in rats as follows: 0/50 control females, 2/50 females given 1.7 mg/kg daily, 7/49 females given 9.8 mg/kg daily, and 9/50 females given 44 mg/kg daily. The occurrence of these neoplasms is probably attributable to the high estrogen/progesterone ratio which occurs in rats as a result of the prolactin-inhibiting action of bromocriptine mesylate. The endocrine mechanisms believed to be involved in the rats are not present in humans. There is no known correlation between uterine malignancies occurring in bromocriptine-treated rats and human risk. In contrast to the findings in rats, the uteri from mice killed after 74 weeks of treatment did not exhibit evidence of drug-related changes.

Bromocriptine mesylate was evaluated for mutagenic potential in the battery of tests that included Ames bacterial mutation assay, mutagenic activity in vitro on V79 Chinese hamster fibroblasts, cytogenetic analysis of Chinese hamster bone marrow cells following in vivo treatment, and an in vivo micronucleus test for mutagenic potential in mice.

No mutagenic effects were obtained in any of these tests.

Fertility and reproductive performance in female rats were not influenced adversely by treatment with bromocriptine beyond the predicted decrease in the weight of pups due to suppression of lactation. In males treated with 50 mg/kg of this drug, mating and fertility were within the normal range. Increased perinatal loss was produced in the subgroups of dams, sacrificed on day 21 postpartum (p.p.) after mating with males treated with the highest dose (50 mg/kg).

PREGNANCY

Category B: Administration of 10-30 mg/kg of bromocriptine to 2 strains of rats on days 6 to 15 postcoitum (p.c.) as well as a single dose of 10 mg/kg on day 5 p.c. interfered with nidation. Three mg/kg given on days 6 to 15 were without effect on nidation, and did not produce any anomalies. In animals treated from day 8-15 p.c., i.e., after implantation, 30 mg/kg produced increased prenatal mortality in the form of increased incidence of embryonic resorption. One anomaly, aplasia of spinal vertebrae and ribs, was found in the group of 262 fetuses derived from the dams treated with 30 mg/kg bromocriptine. No fetotoxic effects were found in offspring of dams treated during the peri- or postnatal period.

Two studies were conducted in rabbits (2 strains) to determine the potential to interfere with nidation. Dose levels of 100 or 300 mg/kg/day from day 1 to day 6 p.c. did not adversely affect nidation. The high dose was approximately 63 times the maximum human dose administered in controlled clinical trials (100 mg/day), based on body surface area. In New Zealand white rabbits, some embryo mortality occurred at 300 mg/kg which was a reflection of overt maternal toxicity. Three studies were conducted in 2 strains of rabbits to determine the teratological potential of bromocriptine at dose levels of 3, 10, 30, 100, and 300 mg/kg given from day 6 to day 18 p.c. In 2 studies with the Yellow-silver strain, cleft palate was found in 3 and 2 fetuses at maternally toxic doses of 100 and 300 mg/kg, respectively. One control fetus also exhibited this anomaly. In the third study conducted with New Zealand white rabbits using an identical protocol, no cleft palates were produced.

No teratological or embryotoxic effects of bromocriptine were produced in any of 6 offspring from 6 monkeys at a dose level of 2 mg/kg.

Information concerning 1276 pregnancies in women taking bromocriptine mesylate has been collected. In the majority of cases, bromocriptine mesylate was discontinued within 8 weeks into pregnancy (mean 28.7 days), however, 8 patients received the drug continuously throughout pregnancy. The mean daily dose for all patients was 5.8 mg (range 1-40 mg).

Of these 1276 pregnancies, there were 1088 full-term deliveries (4 stillborn), 145 spontaneous abortions (11.4%), and 28 induced abortions (2.2%). Moreover, 12 extrauterine gravidities and 3 hydatidiform moles (twice in the same patient) caused early termination of pregnancy. These data compare favorably with the abortion rate (11% - 25%) cited for pregnancies induced by clomiphene citrate, menopausal gonadotropin, and chorionic gonadotropin.

Although spontaneous abortions often go unreported, especially prior to 20 weeks of gestation, their frequency has been estimated to be 15%.

The incidence of birth defects in the population at large ranges from 2% - 4.5%. The incidence in 1109 live births from patients receiving bromocriptine is 3.3%.

There is no suggestion that bromocriptine mesylate contributed to the type or incidence of birth defects in this group of infants.

NURSING MOTHERS

Bromocriptine mesylate should not be used during lactation in postpartum women.

PEDIATRIC USE

The safety and effectiveness of bromocriptine for the treatment of prolactin-secreting pituitary adenomas have been established in patients age 16 to adult. No data are available for bromocriptine use in pediatric patients under the age of 8 years. A single 8-year-old patient treated with bromocriptine for a prolactin-secreting pituitary macroadenoma has been reported without therapeutic response.

The use of bromocriptine for the treatment of prolactin-secreting adenomas in pediatric patients in the age group 11 to under 16 years is supported by evidence from well-controlled trials in adults, with additional data in a limited number (n=14) of children and adolescents 11 to 15 years of age with prolactin-secreting pituitary macro- and microadenomas who have been treated with bromocriptine. Of the 14 reported patients, 9 had successful outcomes, 3 partial responses, and 2 failed to respond to bromocriptine treatment. Chronic hypopituitarism complicated macroadenoma treatment in 5 of the responders, both in patients receiving bromocriptine alone and in those who received bromocriptine in combination with surgical treatment and/or pituitary irradiation.

Safety and effectiveness of bromocriptine in pediatric patients have not been established for any other indication listed in the INDICATIONS AND USAGE section.

GERIATRIC USE

Clinical studies for bromocriptine mesylate did not include sufficient numbers of subjects aged 65 and over to determine whether the elderly respond differently from younger subjects. However, other reported clinical experiences, including postmarketing reporting of adverse events, have not identified differences in response or tolerability between elderly and younger patients. Even though no variation in efficacy or adverse reaction profile in geriatric patients taking bromocriptine mesylate has been observed, greater sensitivity of some elderly individuals cannot be categorically ruled out. In general, dose selection for an elderly patient should be cautious, starting at the lower end of the dose range, reflecting the greater frequency of decreased hepatic, renal or cardiac function, and of concomitant disease or other drug therapy in this population.

ADVERSE REACTIONS

Adverse Reactions from Clinical Trials

Hyperprolactinemic Indications

The incidence of adverse effects is quite high (69%) but these are generally mild to moderate in degree. Therapy was discontinued in approximately 5% of patients because of adverse effects. These in decreasing order of frequency are: nausea (49%), headache (19%), dizziness (17%), fatigue (7%), lightheadedness (5%), vomiting (5%), abdominal cramps (4%), nasal congestion (3%), constipation (3%), diarrhea (3%) and drowsiness (3%).

A slight hypotensive effect may accompany bromocriptine mesylate treatment. The occurrence of adverse reactions may be lessened by temporarily reducing dosage to ½ bromocriptine mesylate tablet 2 or 3 times daily. A few cases of cerebrospinal fluid rhinorrhea have been reported in patients receiving bromocriptine mesylate for treatment of large prolactinomas. This has occurred rarely, usually only in patients who have received previous transsphenoidal surgery, pituitary radiation, or both, and who were receiving bromocriptine mesylate for tumor recurrence. It may also occur in previously untreated patients whose tumor extends into the sphenoid sinus.

Acromegaly

The most frequent adverse reactions encountered in acromegalic patients treated with bromocriptine mesylate were: nausea (18%), constipation (14%), postural/orthostatic hypotension (6%), anorexia (4%), dry mouth/nasal stuffiness (4%), indigestion/dyspepsia (4%), digital vasospasm (3%), drowsiness/tiredness (3%) and vomiting (2%).

Less frequent adverse reactions (less than 2%) were: gastrointestinal bleeding, dizziness, exacerbation of Raynaud’s syndrome, headache and syncope. Rarely (less than 1%) hair loss, alcohol potentiation, faintness, lightheadedness, arrhythmia, ventricular tachycardia, decreased sleep requirement, visual hallucinations, lassitude, shortness of breath, bradycardia, vertigo, paresthesia, sluggishness, vasovagal attack, delusional psychosis, paranoia, insomnia, heavy headedness, reduced tolerance to cold, tingling of ears, facial pallor and muscle cramps have been reported.

Parkinson’s Disease

In clinical trials in which bromocriptine mesylate was administered with concomitant reduction in the dose of levodopa/carbidopa, the most common newly appearing adverse reactions were: nausea, abnormal involuntary movements, hallucinations, confusion, “on-off’’ phenomenon, dizziness, drowsiness, faintness/fainting, vomiting, asthenia, abdominal discomfort, visual disturbance, ataxia, insomnia, depression, hypotension, shortness of breath, constipation, and vertigo.

Less common adverse reactions which may be encountered include: anorexia, anxiety, blepharospasm, dry mouth, dysphagia, edema of the feet and ankles, erythromelalgia, epileptiform seizure, fatigue, headache, lethargy, mottling of skin, nasal stuffiness, nervousness, nightmares, paresthesia, skin rash, urinary frequency, urinary incontinence, urinary retention, and rarely, signs and symptoms of ergotism such as tingling of fingers, cold feet, numbness, muscle cramps of feet and legs or exacerbation of Raynaud’s syndrome.

Abnormalities in laboratory tests may include elevations in blood urea nitrogen, SGOT, SGPT, GGPT, CPK, alkaline phosphatase and uric acid, which are usually transient and not of clinical significance.

Adverse Reactions from Postmarketing Experience

The following adverse reactions have been reported during postapproval use of bromocriptine mesylate (All Indications Combined). Because adverse reactions from spontaneous reports are reported voluntarily from a population of uncertain size, it is generally not possible to reliably estimate their frequency or establish a causal relationship to drug exposure.

Psychiatric disorders: Confusion, psychomotor agitation/excitation, hallucinations, psychotic disorders, insomnia, libido increase, hypersexuality, and impulse control/compulsive behaviors (including gambling, spending, and other intense urges).

Nervous system disorders: Headache, drowsiness, dizziness, dyskinaesia, somnolence, paraesthesia, excess daytime somnolence, sudden onset of sleep.

Eye disorders: Visual disturbance, vision blurred.

Ear and labyrinth disorders: Tinnitus.

Cardiac disorders: Pericardial effusion, constrictive pericarditis, tachycardia, bradycardia, arrhythmia, cardiac valve fibrosis.

Vascular disorders: Hypotension, orthostatic hypotension (very rarely leading to syncope), reversible pallor of fingers and toes induced by cold (especially in patients with history of Raynaud's phenomenon).

Respiratory, thoracic and mediastinal disorders: Nasal congestion, pleural effusion, pleural fibrosis, pleurisy, pulmonary fibrosis, dyspnoea.

Gastrointestinal disorders: Nausea, constipation, vomiting, dry mouth, diarrhea, abdominal pain, retroperitoneal fibrosis, gastrointestinal ulcer, gastrointestinal

hemorrhage.

Skin and subcutaneous tissue disorders: Allergic skin reactions, hair loss.

Musculoskeletal and connective tissue disorders: Leg cramps.

General disorders and administration site conditions: Fatigue, peripheral oedema, a syndrome resembling Neuroleptic Malignant Syndrome on abrupt withdrawal of bromocriptine mesylate, withdrawal symptoms (including apathy, anxiety, depression, fatigue, insomnia, sweating, and pain) with taper or after discontinuation (see Precautions).

Adverse Events Observed in Other Conditions

Postpartum Patients (see above Warnings)

In postpartum studies with bromocriptine mesylate, 23 percent of postpartum patients treated had at least 1 side effect, but they were generally mild to moderate in degree. Therapy was discontinued in approximately 3% of patients. The most frequently occurring adverse reactions were: headache (10%), dizziness (8%), nausea (7%), vomiting (3%), fatigue (1.0%), syncope (0.7%), diarrhea (0.4%) and cramps (0.4%). Decreases in blood pressure (≥ 20 mm Hg systolic and ≥ 10 mm Hg diastolic) occurred in 28% of patients at least once during the first 3 postpartum days; these were usually of a transient nature. Reports of fainting in the puerperium may possibly be related to this effect. In postmarketing experience in the U.S., serious adverse reactions reported include 72 cases of seizures (including 4 cases of status epilepticus), 30 cases of stroke, and 9 cases of myocardial infarction among postpartum patients. Seizure cases were not necessarily accompanied by the development of hypertension. An unremitting and often progressively severe headache, sometimes accompanied by visual disturbance, often preceded by hours to days many cases of seizure and/or stroke. Most patients had shown no evidence of any of the hypertensive disorders of pregnancy including eclampsia, preeclampsia or pregnancy-induced hypertension. One stroke case was associated with sagittal sinus thrombosis, and another was associated with cerebral and cerebellar vasculitis. One case of myocardial infarction was associated with unexplained disseminated intravascular coagulation and a second occurred in conjunction with use of another ergot alkaloid. The relationship of these adverse reactions to bromocriptine mesylate administration has not been established.

In rare cases serious adverse events, including hypertension, myocardial infarction, seizures, stroke, or psychic disorders have been reported in postpartum women treated with bromocriptine mesylate. In some patients the development of seizures or stroke was preceded by severe headache and/or transient visual disturbances. Although the causal relationship of these events to the drug is uncertain, periodic monitoring of blood pressure is advisable in postpartum women receiving bromocriptine mesylate. If hypertension, severe, progressive, or unremitting headache (with or without visual disturbances), or evidence of CNS toxicity develop, the administration of bromocriptine mesylate should be discontinued and the patient should be evaluated promptly.

Particular caution is required in patients who have recently been treated or are on concomitant therapy with drugs that can alter blood pressure, e.g., vasoconstrictors such as sympathomimetics or ergot alkaloids including ergometrine or methylergometrine and their concomitant use in the puerperium is not recommended.

To report SUSPECTED ADVERSE REACTIONS, contact ANI Pharmaceuticals, Inc. at 1-855-204-1431 or FDA at 1-800-FDA-1088 or www.fda.gov/medwatch.

OVERDOSAGE

The most commonly reported signs and symptoms associated with acute bromocriptine mesylate overdose are: nausea, vomiting, constipation, diaphoresis, dizziness, pallor, severe hypotension, malaise, confusion, lethargy, drowsiness, delusions, hallucinations, and repetitive yawning. The lethal dose has not been established and the drug has a very wide margin of safety. However, one death occurred in a patient who committed suicide with an unknown quantity of bromocriptine mesylate and chloroquine.

Treatment of overdose consists of removal of the drug by emesis (if conscious), gastric lavage, activated charcoal, or saline catharsis. Careful supervision and recording of fluid intake and output is essential. Hypotension should be treated by placing the patient in the Trendelenburg position and administering I.V. fluids. If satisfactory relief of hypotension cannot be achieved by using the above measures to their fullest extent, vasopressors should be considered.

There have been isolated reports of children who accidentally ingested bromocriptine mesylate. Vomiting, somnolence and fever were reported as adverse events. Patients recovered either spontaneously within a few hours or after appropriate management.

DOSAGE & ADMINISTRATION

General

It is recommended that bromocriptine mesylate be taken with food. Patients should be evaluated frequently during dose escalation to determine the lowest dosage that produces a therapeutic response.

Hyperprolactinemic Indications

The initial dosage of bromocriptine mesylate tablets in adults is one ½ to one 2½ mg scored tablet daily. An additional 2½ mg tablet may be added to the treatment regimen as tolerated every 2 to 7 days until an optimal therapeutic response is achieved. The therapeutic dosage ranged from 2.5-15 mg daily in adults studied clinically.

Based on limited data in children of age 11 to 15, (see Pediatric Use) the initial dose is one ½ to one 2½ mg scored tablet daily. Dosing may need to be increased as tolerated until a therapeutic response is achieved. The therapeutic dosage ranged from 2.5-10 mg daily in children with prolactin-secreting pituitary adenomas.

In order to reduce the likelihood of prolonged exposure to bromocriptine mesylate should an unsuspected pregnancy occur, a mechanical contraceptive should be used in conjunction with bromocriptine mesylate therapy until normal ovulatory menstrual cycles have been restored. Contraception may then be discontinued in patients desiring pregnancy.

Thereafter, if menstruation does not occur within 3 days of the expected date, bromocriptine mesylate therapy should be discontinued and a pregnancy test performed.

Acromegaly

Virtually all acromegalic patients receiving therapeutic benefit from bromocriptine mesylate also have reductions in circulating levels of growth hormone. Therefore, periodic assessment of circulating levels of growth hormone will, in most cases, serve as a guide in determining the therapeutic potential of bromocriptine mesylate. If, after a brief trial with bromocriptine mesylate therapy, no significant reduction in growth hormone levels has taken place, careful assessment of the clinical features of the disease should be made, and if no change has occurred, dosage adjustment or discontinuation of therapy should be considered.

The initial recommended dosage is one ½ to one 2½ mg bromocriptine mesylate tablet on retiring (with food) for 3 days. An additional one ½ to 1 bromocriptine mesylate tablet should be added to the treatment regimen as tolerated every 3 to 7 days until the patient obtains optimal therapeutic benefit. Patients should be reevaluated monthly and the dosage adjusted based on reductions of growth hormone or clinical response. The usual optimal therapeutic dosage range of bromocriptine mesylate varies from 20-30 mg/day in most patients. The maximal dosage should not exceed 100 mg/day.

Patients treated with pituitary irradiation should be withdrawn from bromocriptine mesylate therapy on a yearly basis to assess both the clinical effects of radiation on the disease process as well as the effects of bromocriptine mesylate therapy. Usually a 4 to 8 week withdrawal period is adequate for this purpose. Recurrence of the signs/symptoms or increases in growth hormone indicate the disease process is still active and further courses of bromocriptine mesylate should be considered.

Parkinson’s Disease

The basic principle of bromocriptine mesylate therapy is to initiate treatment at a low dosage and, on an individual basis, increase the daily dosage slowly until a maximum therapeutic response is achieved. The dosage of levodopa during this introductory period should be maintained, if possible. The initial dose of bromocriptine mesylate is one ½ of a 2½ mg bromocriptine mesylate tablets twice daily with meals. Assessments are advised at 2-week intervals during dosage titration to ensure that the lowest dosage producing an optimal therapeutic response is not exceeded. If necessary, the dosage may be increased every 14 to 28 days by 2½ mg/day with meals. Should it be advisable to reduce the dosage of levodopa because of adverse reactions, the daily dosage of bromocriptine mesylate if increased, should be accomplished gradually in small (2½ mg) increments.

The safety of bromocriptine mesylate has not been demonstrated in dosages exceeding 100 mg/day.

HOW SUPPLIED

Bromocriptine Mesylate Tablets, USP 2.5 mg

Bromocriptine mesylate tablets are available in bottles containing 30 and 100 tablets of 2.5 mg, each bottle contains a desiccant.

Off-white, round, flat-faced, beveled-edge tablets, debossed “E” above the score and “280” below the score on one side and debossed “2.5” on the other side, each containing 2.5 mg bromocriptine (as the mesylate).

Bottles of 30: NDC 70954-978-10

Bottles of 100: NDC 70954-978-20

Store and Dispense

Store at 68ºF to 77ºF (20ºC to 25ºC); excursions permitted to 59ºF to 86ºF (15ºC to 30ºC) [See USP Controlled Room Temperature].

Dispense in a tight, light-resistant container.

Manufactured by:

Esjay Pharma Private Limited,

India

Distributed by:

ANI Pharmaceuticals, Inc.

Baudette, MN 56623

P3309/00/25

Rev. 04/2025

PACKAGE LABEL.PRINCIPAL DISPLAY PANEL

NDC 70954-978-10 Bottle of 30 tablets

NDC 70954-978-20 Bottle of 100 tablets